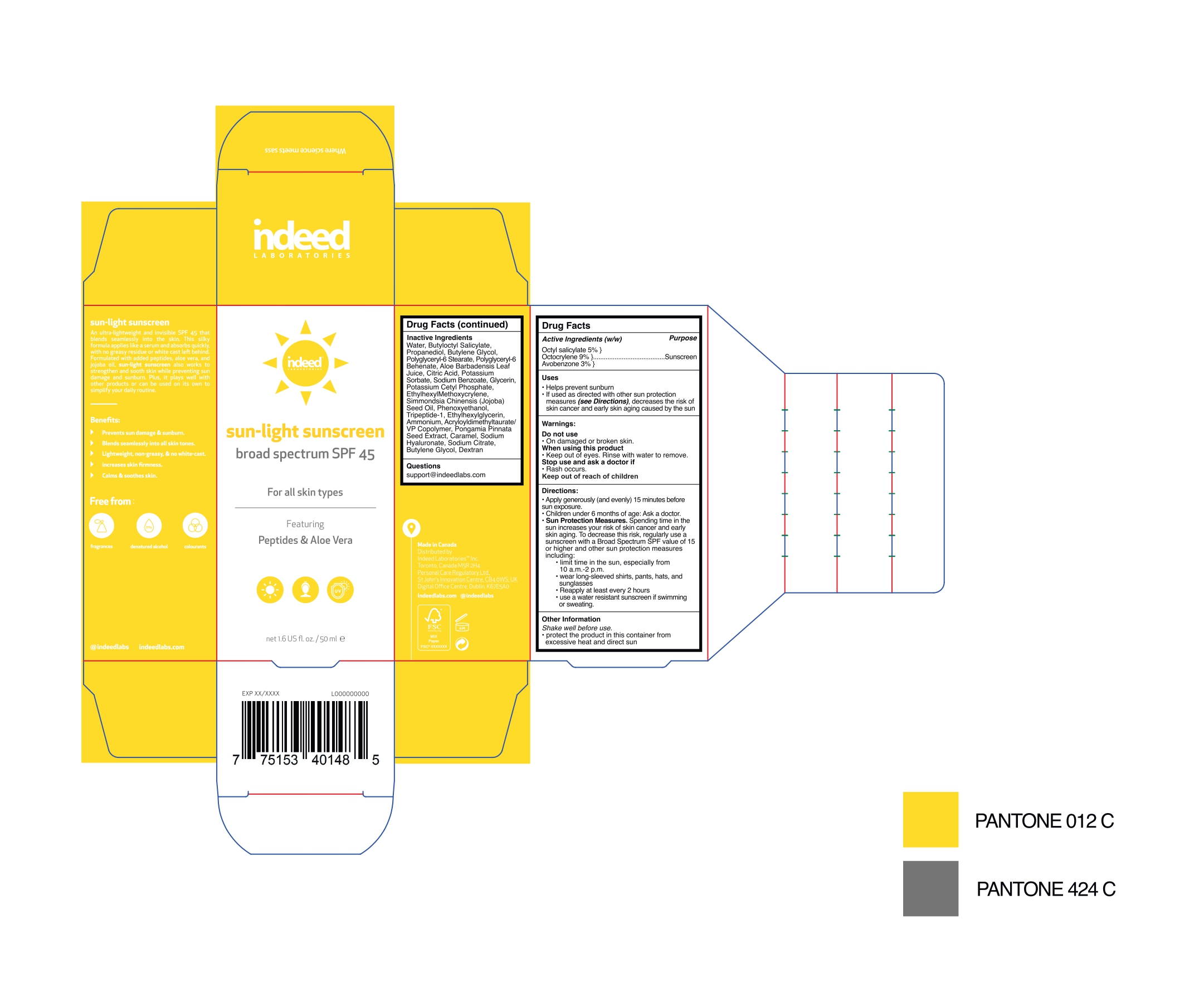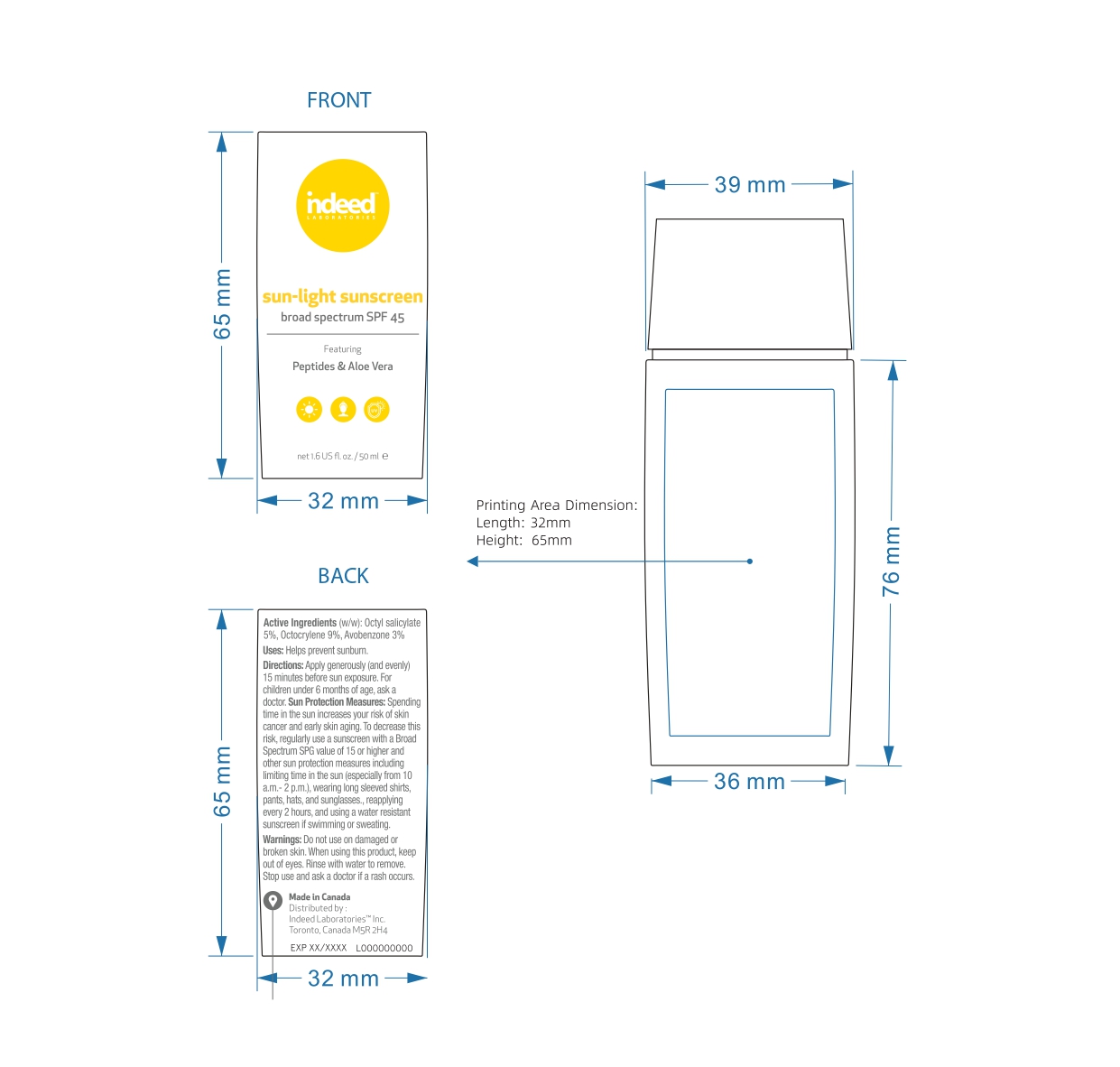 DRUG LABEL: Sun-Light Sunscreen
NDC: 83407-001 | Form: LOTION
Manufacturer: Indeed Laboratories Inc.
Category: otc | Type: HUMAN OTC DRUG LABEL
Date: 20230523

ACTIVE INGREDIENTS: OCTOCRYLENE 9 mg/1 mL; OCTISALATE 5 mg/1 mL; AVOBENZONE 3 mg/1 mL
INACTIVE INGREDIENTS: WATER; GLYCERIN; BUTYLENE GLYCOL; ALOE VERA LEAF; PROPANEDIOL; ETHYLHEXYLGLYCERIN; JOJOBA OIL; PHENOXYETHANOL; BUTYLOCTYL SALICYLATE; POLYGLYCERYL-6 BEHENATE; ANHYDROUS CITRIC ACID; PONGAMIA PINNATA SEED; POTASSIUM SORBATE; POLYGLYCERYL-6 STEARATE; DEXTRAN 110; CARAMEL; HYALURONATE SODIUM; PREZATIDE; TRISODIUM CITRATE DIHYDRATE; ETHYLHEXYL METHOXYCRYLENE; POTASSIUM CETYL PHOSPHATE; AMMONIUM ACRYLOYLDIMETHYLTAURATE/VP COPOLYMER; SODIUM BENZOATE

Sun-light Sunscreen SPF 45 Indeed

PACKAGE LABEL

Active Ingredient

Octyl salicylate 5%

Octocrylene 9%

Avobenzone 3%

Purpose

Sunscreen

Warnings

Do not use

- On damaged or broken skin.

When using this product
- Keep out of eyes. Rinse with water to remove.

Stop use and ask a doctor if

- Rash occurs.

Keep out of reach of children

Keep out of reach of children.

Directions

- Apply generously (and evenly) 15 minutes before sun exposure.

- Children under 6 months of age: Ask a doctor.

- Sun protection measures. Spending time in the sun increases your risk of skin cancer and early skin aging. To decrease this risk, regularly use a sunscreen with a Broad Spectrum SPF value of 15 or higher and other sun protection measures including:

- limit time in the sun, especially from 10 a.m.-2p.m.

- wear long sleeve shirts, pants, hats and sunglasses.

- reapply at least every 2 hours

- use a water resistant sunscreen if swimming or sweating.

Indications and Usage

Uses

- Helps prevent sunburn.

- If used as directed with other sun protection measures (see Directions), decreases the risk of skin cancer and early skin aging caused by the sun.

Inactive ingredients

Water, Butyloctyl salicylate, propanediol, butylene glycol, polyglyceryl-6 stearate, polyglyceryl-6 behenate, aloe barbadensis leaf juice, citric acid, potassium sorbate, sodium benzoate, glycerin, potassium cetyl phosphate, ethylhexylmethoxycrylene, Simmondsia chinensis (jojoba) seed oil, phenoxyethanol, tripeptide-1, ethylhexylglycerin, ammonium, acryloyldimethyltaurate/VP copolymer, Pongamia pinnata seed extradct, caramel, sodium hyaluronate, sodium citrate, butylene glycol, dextran.